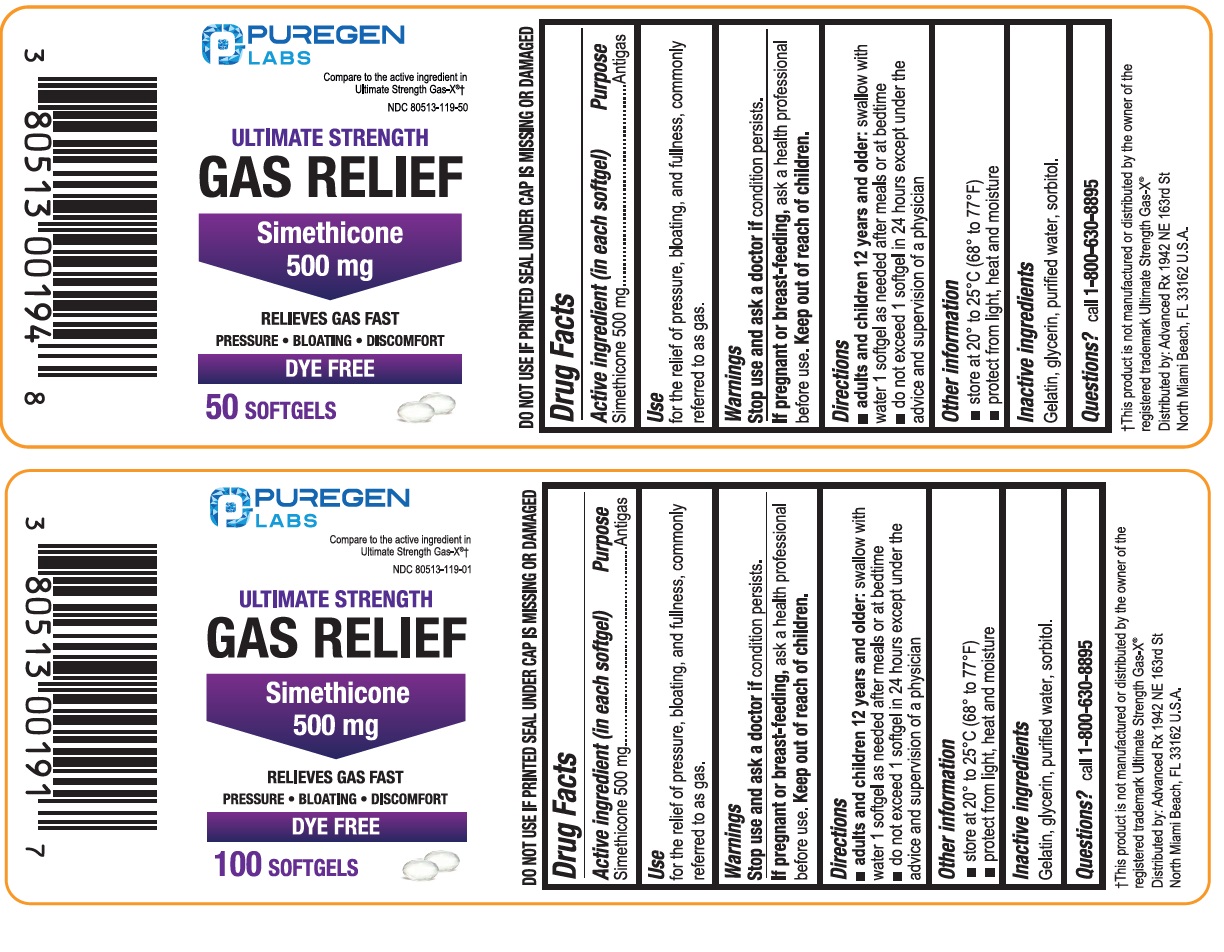 DRUG LABEL: Gas Relief

NDC: 80513-119 | Form: CAPSULE, LIQUID FILLED
Manufacturer: Advanced Rx LLC
Category: otc | Type: HUMAN OTC DRUG LABEL
Date: 20260201

ACTIVE INGREDIENTS: DIMETHICONE, UNSPECIFIED 500 mg/1 1
INACTIVE INGREDIENTS: GELATIN, UNSPECIFIED; GLYCERIN; WATER; SORBITOL

ULTIMATE STRENGTH GAS RELIEF- simethicone capsule, liquid filled

Active ingredient (in each softgel)

Simethicone 500 mg

Purpose

Antigas

Use

for the relief of pressure, bloating, and fullness, commonly referred to as gas.

Warning

Stop use and ask a doctor if

condition persists.

If pregnant or breast-feeding,

ask a health professional before use.

Directions

- adults and children 12 years and older:swallow with water 1 softgel as needed after meals or at bedtime
- do not exceed 1 softgel in 24 hours except under the advice and supervision of a physician

Other information

- store at 20º to 25ºC (68º to 77ºF)
- protect from light, heat and moisture

Inactive ingredients

Gelatin, glycerin, purified water, sorbitol.

Questions?

call 1-800-630-8895